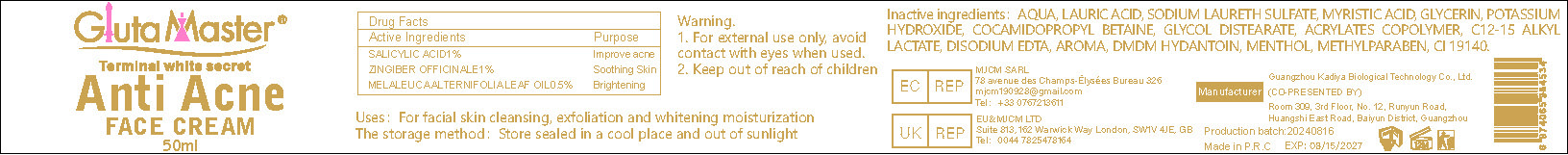 DRUG LABEL: Anti Acne FACECREAM
NDC: 84423-036 | Form: CREAM
Manufacturer: Guangzhou Kadiya Biotechnology Co., Ltd.
Category: otc | Type: HUMAN OTC DRUG LABEL
Date: 20240826

ACTIVE INGREDIENTS: SALICYLIC ACID 0.5 mg/50 mL; MELALEUCA ALTERNIFOLIA LEAF 0.25 mg/50 mL; ZINGIBER OFFICINALE WHOLE 0.5 mg/50 mL
INACTIVE INGREDIENTS: TRISILOXANE; METHYLPARABEN; HEXAMIDINE DIISETHIONATE; CETEARYL GLUCOSIDE; CETOSTEARYL ALCOHOL; BUTYLENE GLYCOL; IODOPROPYNYL BUTYLCARBAMATE; MINERAL OIL; GLYCERYL MONOSTEARATE; DMDM HYDANTOIN; BORNEOL; TRIDECETH-6; WATER; HYDROGENATED PALM KERNEL OIL; GLYCERIN; ALLANTOIN; MENTHOL; HYALURONIC ACID; EDETATE DISODIUM; MEDIUM-CHAIN TRIGLYCERIDES; GLYCYRRHIZINATE DIPOTASSIUM; XANTHAN GUM; FD&C YELLOW NO. 5; PEG-100 STEARATE; PROPYLENE GLYCOL; ISONONYL ISONONANOATE; HYDROXYETHYL ACRYLATE/SODIUM ACRYLOYLDIMETHYL TAURATE COPOLYMER (45000 MPA.S AT 1%)

PURPOSE

For the improvement and lightening of redness on the face

INACTIVE INGREDIENT

AQUA、MINERAL OIL、GLYCERIN、PROPYLENE GLYCOL、CETEARYL ALCOHOL、HYDROGENATED PALM KERNEL OIL、ISONONYL ISONONANOATE、CAPRYLIC/CAPRIC、TRIGLYCERIDE、TRISILOXANE、GLYCERYL STEARATE、HYDROXYETHYL ACRYLATE/SODIUM ACRYLOYLDIMETHYL TAURATE COPOLYMER、CETEARYL GLUCOSIDE、PEG-100 LANOLIN、DMDM HYDANTOIN、MENTHOL、ALLANTOIN、METHYLPARABEN、BORNEOL、HEXAMIDINE DIISETHIONATE、DIPOTASSIUM GLYCYRRHIZATE、AROMA、XANTHAN GUM、TRIDECETH-6、HYALURONIC ACID、BUTYLENE GLYCOL、DISODIUM EDTA、IODOPROPYNYL BUTYLCARBAMATE、CI 19140

WARNINGS

1、For external use only, avoid contact with eyes when used
2、Keep out of reach of children

INDICATIONS AND USAGE

For facial skin cleansing, exfoliation and whitening moisturization

DOSAGE AND ADMINISTRATION

For facial skin cleansing, exfoliation and whitening moisturization

Active Ingredients
SALICYLIC ACID1%
ZINGIBER OFFICINALE1%
MELALEUCA ALTERNIFOLIA LEAF OIL0.5%

KEEP OUT OF REACH OF CHILDREN SECTION

PACKAGE LABEL

Active Ingredients
SALICYLIC ACID1%
ZINGIBER OFFICINALE1%
MELALEUCA ALTERNIFOLIA LEAF OIL0.5%

Uses：
For the improvement and lightening of redness on the face
The storage method：
Store sealed in a cool place and out of sunlight

Warning.
1、For external use only, avoid contact with eyes when used
2、Keep out of reach of children

Inactive ingredients：
AQUA、MINERAL OIL、GLYCERIN、PROPYLENE GLYCOL、CETEARYL ALCOHOL、HYDROGENATED PALM KERNEL OIL、ISONONYL ISONONANOATE、CAPRYLIC/CAPRIC、TRIGLYCERIDE、TRISILOXANE、GLYCERYL STEARATE、HYDROXYETHYL ACRYLATE/SODIUM ACRYLOYLDIMETHYL TAURATE COPOLYMER、CETEARYL GLUCOSIDE、PEG-100 LANOLIN、DMDM HYDANTOIN、MENTHOL、ALLANTOIN、METHYLPARABEN、BORNEOL、HEXAMIDINE DIISETHIONATE、DIPOTASSIUM GLYCYRRHIZATE、AROMA、XANTHAN GUM、TRIDECETH-6、HYALURONIC ACID、BUTYLENE GLYCOL、DISODIUM EDTA、IODOPROPYNYL BUTYLCARBAMATE、CI 19140